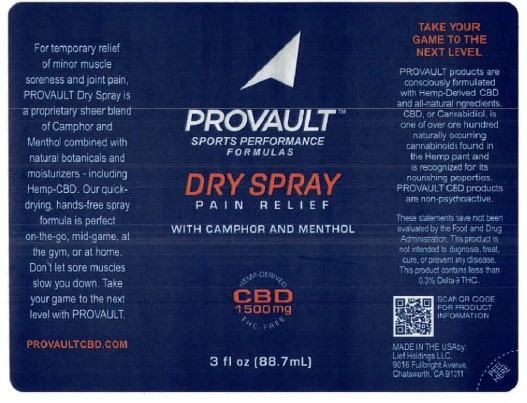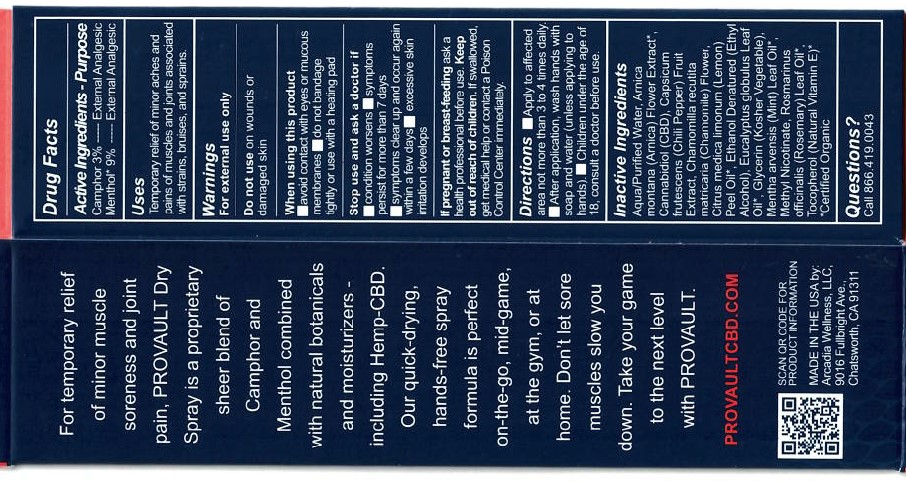 DRUG LABEL: Provault DrySpray CBD Pain Relief
NDC: 61577-6000 | Form: SPRAY
Manufacturer: Sombra Cosmetics Inc
Category: otc | Type: HUMAN OTC DRUG LABEL
Date: 20221018

ACTIVE INGREDIENTS: MENTHOL .09 g/1 g; CAMPHOR (SYNTHETIC) .02 g/1 g
INACTIVE INGREDIENTS: WATER; GLYCERIN; CANNABIDIOL; CAPSAICIN; TOCOPHEROL; ROSEMARY OIL; LEMON OIL; CHAMOMILE; ALCOHOL; EUCALYPTUS OIL; MENTHA ARVENSIS FLOWER OIL; ARNICA MONTANA FLOWER WATER; METHYL NICOTINATE

Provault DrySpray CBD Pain Relief

Active Ingredients

Menthol USP 9%, Camphor USP 2%

Purpose

External Analgesic

Keep out of reach of children

Uses

Temporary relief of monor aches and pains of muscles and joints associated with strains, bruises and sprains.

Warnings

For external use only.

Directions

Apply to affected area not more than 3 to 4 times daily. After each application, wash hands with soap and water (unless applying to hands). Children under the age of 18, consult a doctor before use.

Inactive Ingredients

Aqua/Purified water, Arnica Montana (arnica) Flower Extract, Cannabidiol (CBD), Capsicum Frutescens (Chili Pepper) Friut Extract, Chamomilla Recutita Matricaria (Chamomile) Flower, Citrus medica Limonum (Lemon) Peel Oil, Ethanol Denatured (Ethyl Alcohol), Eucalyptus Globulus Leaf Oil, Glycerin (Kosher Vegetable), Mentha Avensis (Mint) Leaf Oil, Metyl Nicotinate, Rosmarinus Officinalis (Rosemary) Leaf Oil, Tocopherol (Natural Vitamin E).

Questions or Comments

Call 866 419 0043